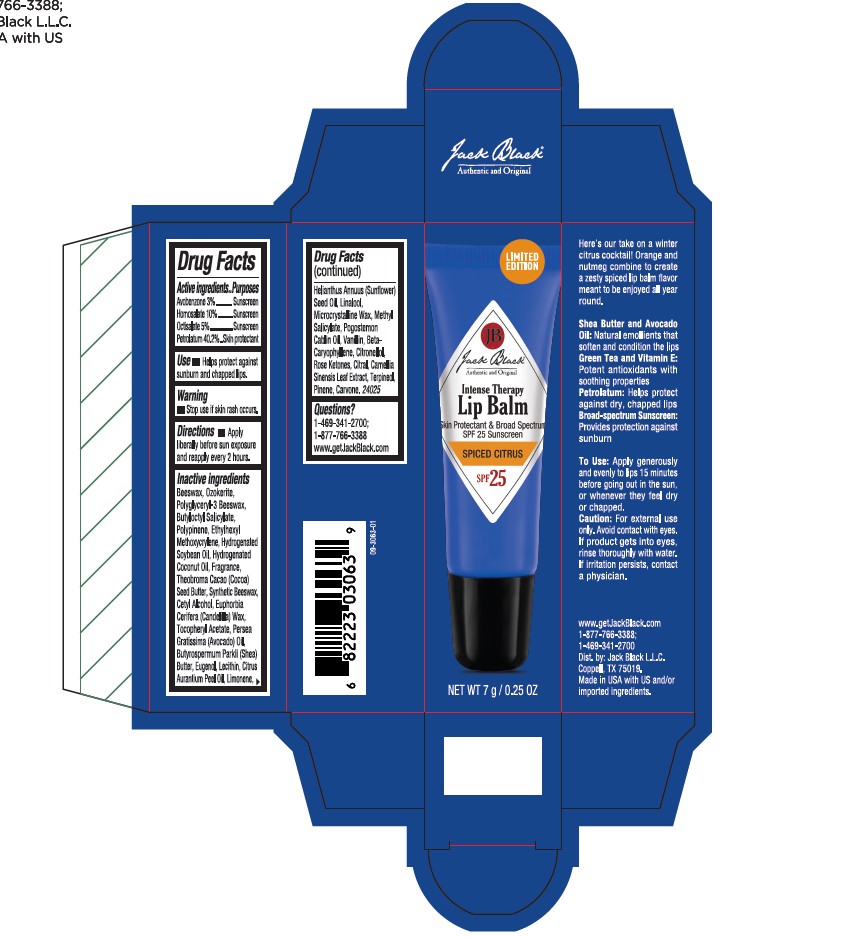 DRUG LABEL: Jack Black
NDC: 66738-171 | Form: OINTMENT
Manufacturer: Jack Black L.L.C.
Category: otc | Type: HUMAN OTC DRUG LABEL
Date: 20250905

ACTIVE INGREDIENTS: OCTISALATE 5 g/100 mL; AVOBENZONE 3 g/100 mL; HOMOSALATE 10 g/100 mL; PETROLATUM 40.2 g/100 mL
INACTIVE INGREDIENTS: CITRAL; PINENE; ETHYLHEXYL METHOXYCRYLENE; EUPHORBIA CERIFERA (CANDELILLA) WAX; CITRONELLOL; TERPINEOL; METHYL SALICYLATE; POLYGLYCERYL-3 BEESWAX; LINALOOL; BETA-CARYOPHYLLENE; HYDROGENATED SOYBEAN OIL; EUGENOL; HELIANTHUS ANNUUS (SUNFLOWER) SEED OIL; THEOBROMA CACAO (COCOA) SEED BUTTER; BEESWAX; CAMELLIA SINENSIS LEAF; SYNTHETIC BEESWAX; CETYL ALCOHOL; BUTYROSPERMUM PARKII (SHEA) BUTTER; VANILLIN; CITRUS AURANTIUM PEEL OIL; LIMONENE, (+)-; .ALPHA.-TOCOPHEROL ACETATE; CERESIN; PERSEA GRATISSIMA (AVOCADO) OIL; HYDROGENATED COCONUT OIL; BUTYLOCTYL SALICYLATE; MICROCRYSTALLINE WAX; POGOSTEMON CABLIN OIL; CARVONE

spiced citrus

Active ingredients

Avobenzone 3%
Homosalate 10%
Octisalate 5%
Petrolatum 40.2%

Purposes

Sunscreen

Sunscreen

Sunscreen

Skin protectant

Use

• Helps protect against sunburn and chapped lips.

Warning

Stop use if skin rash occurs.

Keep out of reach of children.

Directions

• Apply liberally before sun exposure and reapply every 2 hours.

Inactive ingredients

Beeswax, Ozokerite, Polyglyceryl-3 Beeswax, Butyloctyl Salicylate, Polypinene, Ethylhexyl Methoxycrylene, Hydrogenated Soybean Oil, Hydrogenated Coconut Oil, Fragrance, Theobroma Cacao (Cocoa) Seed Butter, Synthetic Beeswax, Cetyl Alcohol, Euphorbia Cerifera (Candelilla) Wax, Tocopheryl Acetate, Persea Gratissima (Avocado) Oil, Butyrospermum Parkii (Shea) Butter, Eugenol, Lecithin, Citrus Aurantium Peel Oil, Limonene, Helianthus Annuus (Sunflower) Seed Oil, Linalool, Microcrystalline Wax, Methyl Salicylate, Pogostemon Cablin Oil, Vanillin, beta-Caryophyllene, Citronellol, Rose Ketones, Citral, Camellia Sinensis Leaf Extract, Terpineol, Pinene, Carvone

Questions?

1-469-341-2700; 1-877-766-3388 www.getJackBlack.com